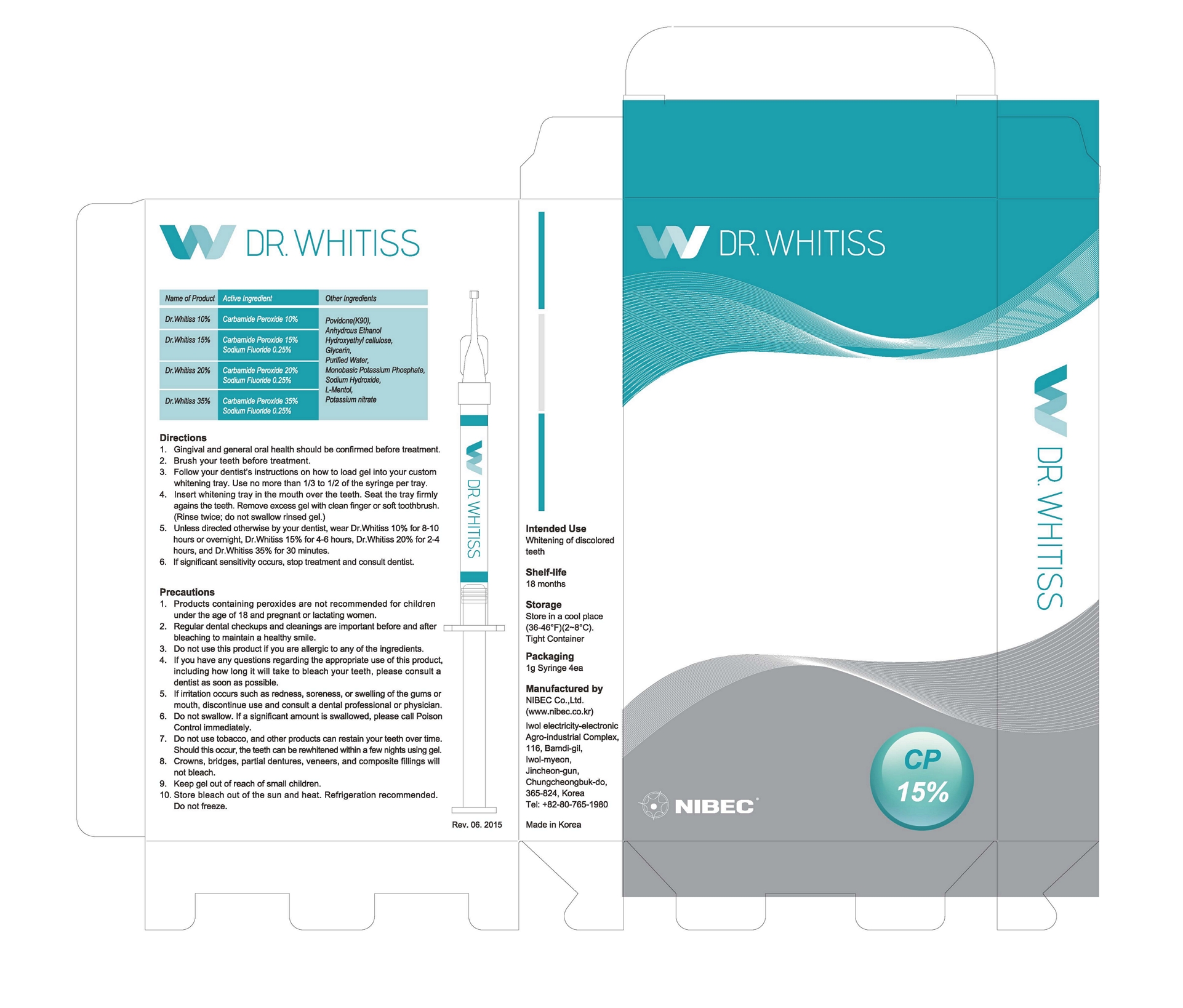 DRUG LABEL: Dr.Whitiss 15%
NDC: 47649-1401 | Form: GEL, DENTIFRICE
Manufacturer: NIBEC Co., Ltd.
Category: otc | Type: HUMAN OTC DRUG LABEL
Date: 20230105

ACTIVE INGREDIENTS: CARBAMIDE PEROXIDE 150 mg/1 g; SODIUM FLUORIDE 2.5 mg/1 g
INACTIVE INGREDIENTS: POVIDONE K90; GLYCERIN; WATER; POTASSIUM NITRATE; POTASSIUM PHOSPHATE, MONOBASIC; LEVOMENTHOL; HYDROXYETHYL CELLULOSE (2000 CPS AT 1%); SODIUM HYDROXIDE; ALCOHOL

Drug Facts

ACTIVE INGREDIENT

Carbamide Peroxide 15%

Sodium Fluoride 0.25%

INACTIVE INGREDIENT

Povidone (K90), Anhydrous Ethanol, Hydroxyethyl Cellulose, Glycerin, Purified Water, Monobasic Potassium Phosphate, Sodium Hydroxide, L-Menthol, Potassium Nitrate

PURPOSE

Whitening of discolored teeth

Keep gel out of reach of small children.

INDICATIONS AND USAGE

1. Gingival and general oral heath should be confirmed before treatment.
2. Brush your teeth before treatment.
3. Follow your dentist’s instructions on how to load gel into your custom whitening tray. Use no more than 1/3 to 1/2 of the syringe per tray.
4. Insert whitening tray in the mouth over the teeth. Seat the tray firmly agains the teeth. Remove excess gel with clean finger or soft toothbrush.(Rinse twice; do not swallow rinsed gel.)
5. Unless directed otherwise by your dentist, wear Dr.Whitiss 10% for 8-10 hours or overnight, Dr.Whitiss 15% for 4-6 hours, Dr.Whitiss20% for 2-4 hours, and Dr.Whitiss 35% for 30 minutes.
6. If significant sensitivity occurs, stop treatment and consult dentist.

WARNINGS

1. Products containing peroxides are not recommended for children under the age of 18 and pregnant or lactating women.

2. Regular dental checkups and cleanings are important before and after bleaching to maintain a healthy smile.

3. Do not use this product if you are allergic to any of the ingredients.

4. If you have any questions regarding the appropriate use of this product, including how long it will take to bleach your teeth, please consult a dentist as soon as possible.

5. If irritation occurs such as redness, soreness, or swelling of the gums or mouth, discontinue use and consult a dental professional or physician.

6. Do not swallow. If a significant amount is swallowed, please call Poison Control immediately.

7. Do not use tobacco, and other products can restain your teeth over time. Should this occur, the teeth can be rewhitened within a few nights using gel.

8. Crowns, bridges, partial dentures, veneers, and composite fillings will not bleach.

9. Keep gel out of reach of small children.

10. Store bleach out of the sun and heat. Refrigeration recommended. Do not freeze.

DOSAGE AND ADMINISTRATION

for dental use only